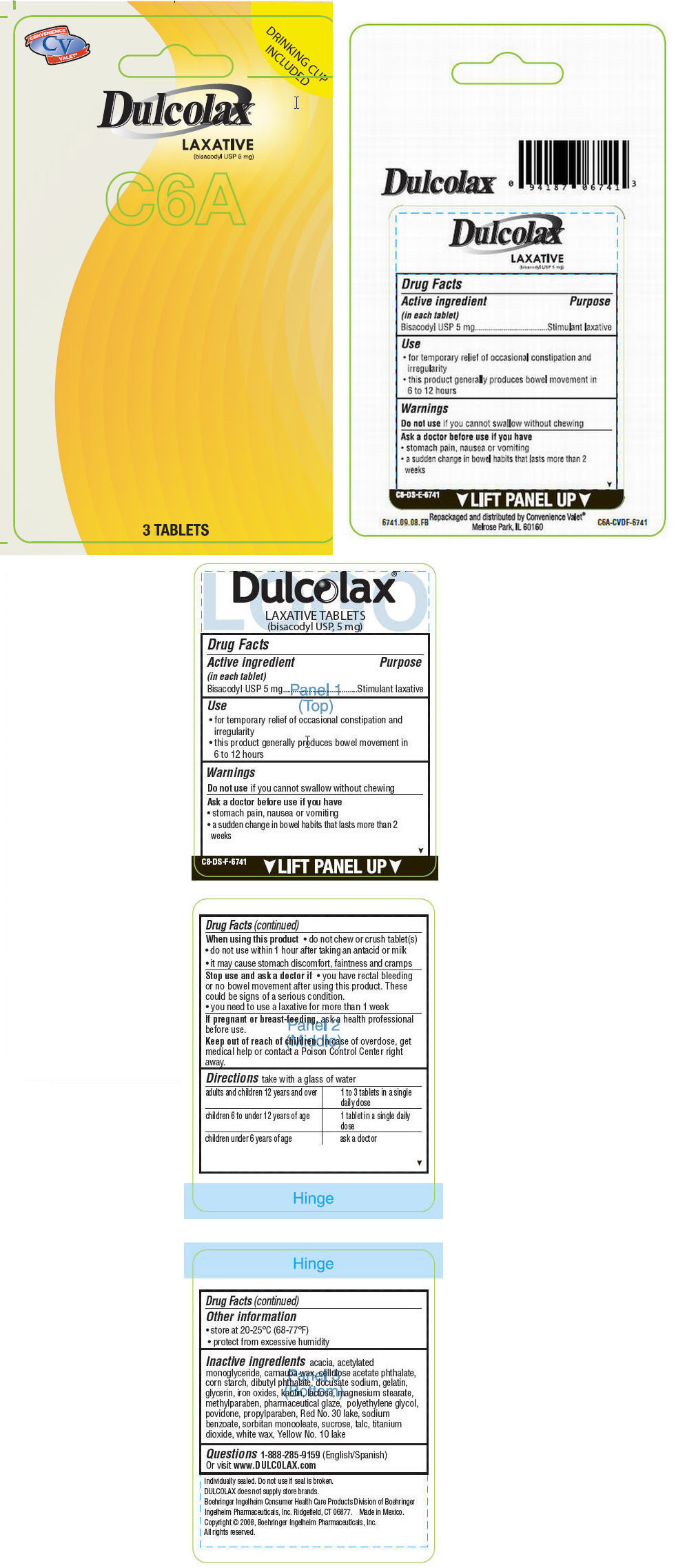 DRUG LABEL: Dulcolax
NDC: 29485-6741 | Form: TABLET, COATED
Manufacturer: Mechanical Servants, Inc.
Category: otc | Type: HUMAN OTC DRUG LABEL
Date: 20120106

ACTIVE INGREDIENTS: bisacodyl 5 mg/1 1
INACTIVE INGREDIENTS: acacia; carnauba wax; cellacefate; starch, corn; dibutyl phthalate; docusate sodium; gelatin; glycerin; kaolin; lactose; magnesium stearate; methylparaben; shellac; polyethylene glycols; povidone; propylparaben; sodium benzoate; sorbitan monooleate; sucrose; talc; titanium dioxide; white wax; diacetylated monoglycerides; FERRIC OXIDE RED

Dulcolax®

Drug Facts

Active ingredient (in each tablet)

Bisacodyl USP 5 mg

Purpose

Stimulant laxative

Use

- for temporary relief of occasional constipation and irregularity
- this product generally produces bowel movement in 6 to 12 hours

Warnings

Do not use if you cannot swallow without chewing

Ask a doctor before use if you have

- stomach pain, nausea or vomiting
- a sudden change in bowel habits that lasts more than 2 weeks

When using this product

- do not chew or crush tablet(s)
- do not use within 1 hour after taking an antacid or milk
- it may cause stomach discomfort, faintness and cramps

Stop use and ask a doctor if

- you have rectal bleeding or no bowel movement after using this product. These could be signs of a serious condition.
- you need to use a laxative for more than 1 week

PREGNANCY OR BREAST FEEDING

If pregnant or breast-feeding, ask a health professional before use.

Keep out of reach of children. In case of overdose, get medical help or contact a Poison Control Center right away.

Directions

take with a glass of water

adults and children 12 years and over | 1 to 3 tablets in a single daily dose
children 6 to under 12 years of age | 1 tablet in a single daily dose
children under 6 years of age | ask a doctor

Other information

- store at 20-25°C (68-77°F)
- protect from excessive humidity

Inactive ingredients

acacia, acetylated monoglyceride, carnauba wax, cellulose acetate phthalate, corn starch, dibutyl phthalate, docusate sodium, gelatin, glycerin, iron oxides, kaolin, lactose, magnesium stearate, methylparaben, pharmaceutical glaze, polyethylene glycol, povidone, propylparaben, Red No. 30 lake, sodium benzoate, sorbitan monooleate, sucrose, talc, titanium dioxide, white wax, Yellow No. 10 lake

Questions

1-888-285-9159 (English/Spanish)

Or visit www.DULCOLAX.com

Repackaged and distributed by Convenience Valet® Melrose Park, IL 60160

PRINCIPAL DISPLAY PANEL - 5 mg Pouch Package

CONVENIENCE
CV
VALET®

DRINKING CUP
INCLUDED

Dulcolax®
LAXATIVE
(bisacodyl USP 5 mg)
C6A

3 TABLETS